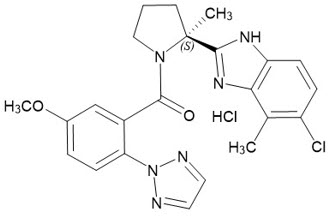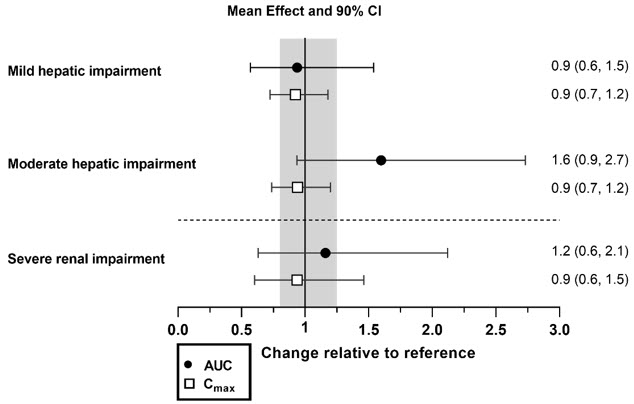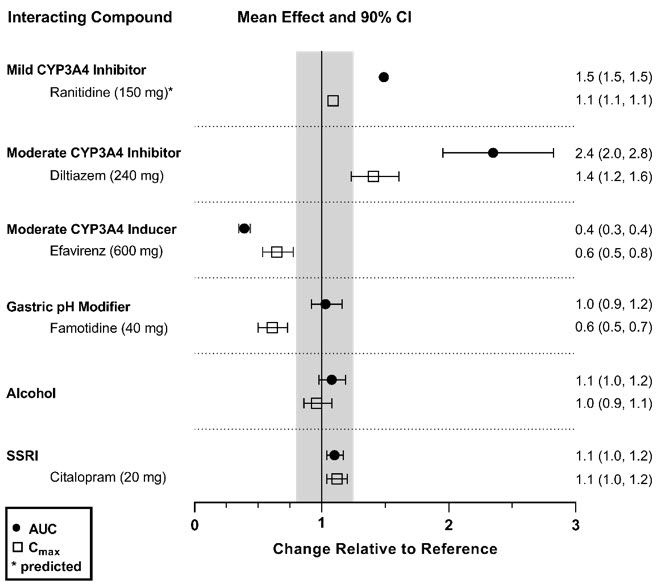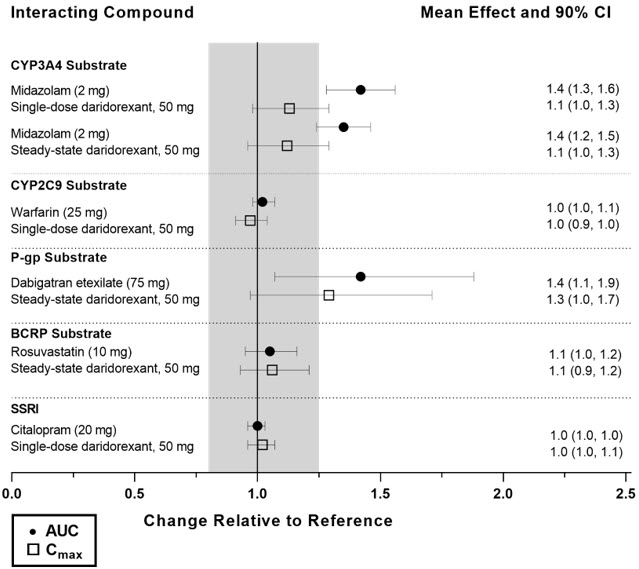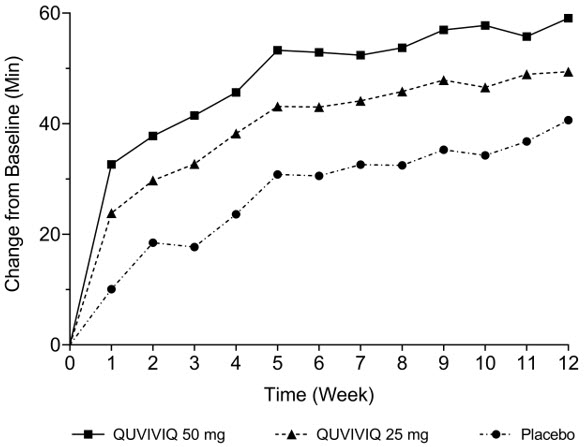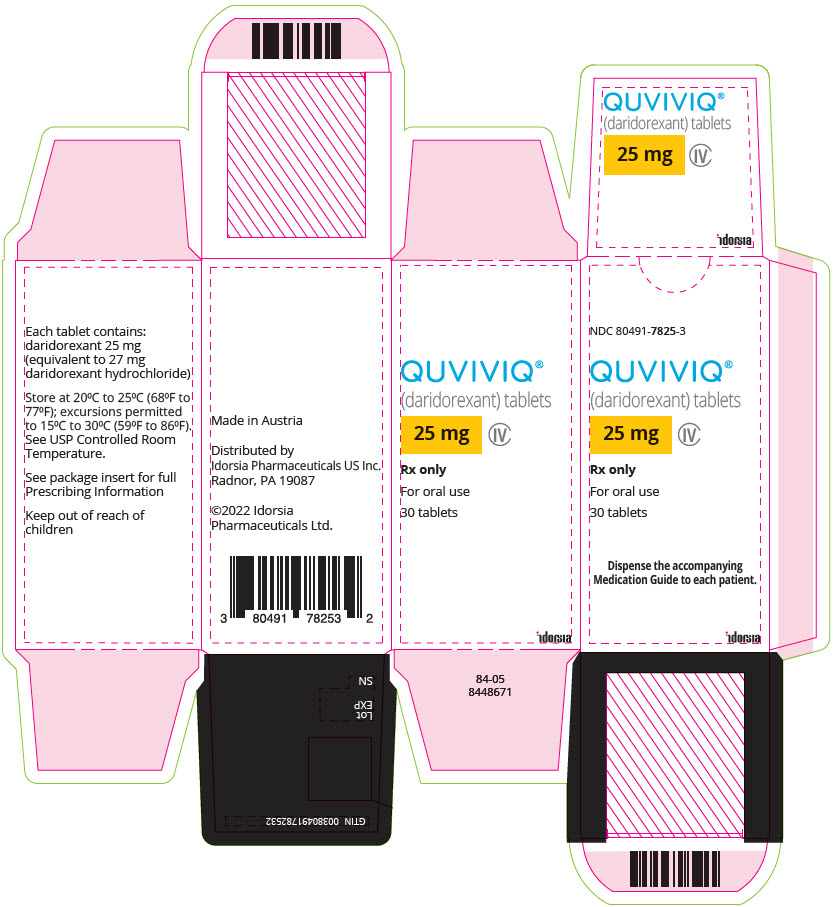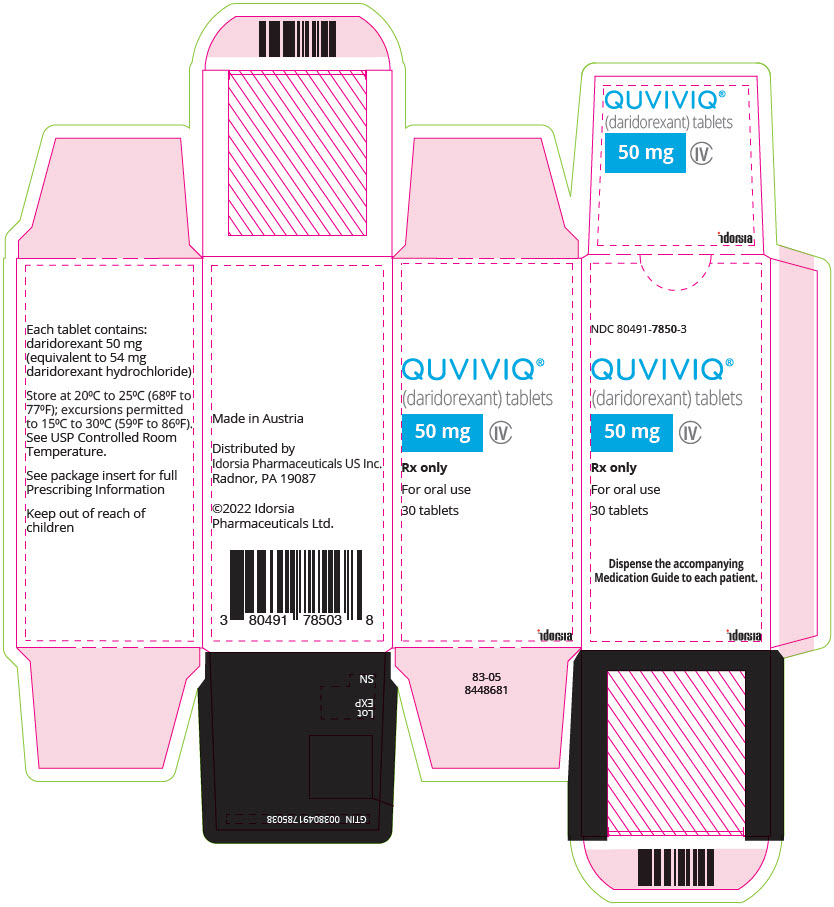 DRUG LABEL: QUVIVIQ
NDC: 80491-7825 | Form: TABLET, FILM COATED
Manufacturer: Idorsia Pharmaceuticals Ltd
Category: prescription | Type: HUMAN PRESCRIPTION DRUG LABEL
Date: 20260226
DEA Schedule: CIV

ACTIVE INGREDIENTS: daridorexant 25 mg/1 1
INACTIVE INGREDIENTS: Mannitol; MICROCRYSTALLINE CELLULOSE 101; Povidone K30; WATER; Silicon dioxide; Magnesium stearate; MICROCRYSTALLINE CELLULOSE 102; HYPROMELLOSE, UNSPECIFIED; GLYCERIN; Talc; Titanium dioxide; FERRIC OXIDE RED; FERROSOFERRIC OXIDE

HIGHLIGHTS OF PRESCRIBING INFORMATION

These highlights do not include all the information needed to use QUVIVIQ safely and effectively. See full prescribing information for QUVIVIQ.
QUVIVIQ (daridorexant) tablets, for oral use, CIV
Initial U.S. Approval: 2022

RECENT MAJOR CHANGES

Contraindications (4) | 10/2023
Warnings and Precautions (5.5) | 9/2024

1 INDICATIONS AND USAGE

QUVIVIQ is an orexin receptor antagonist indicated for the treatment of adult patients with insomnia, characterized by difficulties with sleep onset and/or sleep maintenance. (1)

2 DOSAGE AND ADMINISTRATION

- The recommended dosage is 25 mg to 50 mg once per night, taken orally within 30 minutes before going to bed, with at least 7 hours remaining prior to planned awakening. (2.1)
- Time to sleep onset may be delayed if taken with or soon after a meal. (2.1)
- Hepatic Impairment: (2.3)
  - Moderate hepatic impairment: Maximum recommended dosage is 25 mg no more than once per night.
  - Severe hepatic impairment: Not recommended.

3 DOSAGE FORMS AND STRENGTHS

Tablets: 25 mg, 50 mg. (3)

4 CONTRAINDICATIONS

- Narcolepsy. (4)
- Known hypersensitivity to daridorexant or other components of QUVIVIQ. (4)

5 WARNINGS AND PRECAUTIONS

- CNS-Depressant Effects and Daytime Impairment: Impairs alertness and motor coordination including morning impairment. Risk increases when used with other central nervous system (CNS) depressants. For patients taking QUVIVIQ, caution against next-day driving and other activities requiring complete mental alertness. (5.1)
- Worsening of Depression/Suicidal Ideation: Worsening of depression or suicidal thinking may occur. (5.2)
- Sleep Paralysis, Hypnagogic/Hypnopompic Hallucinations, and Cataplexy-like Symptoms: May occur with use of QUVIVIQ. (5.3)
- Complex Sleep Behaviors: Behaviors including sleepwalking, sleep driving, and engaging in other activities while not fully awake may occur. Discontinue immediately if complex sleep behavior occurs. (5.4)
- Compromised Respiratory Function: Effect on respiratory function should be considered. (5.5, 8.7)
- Need to Evaluate for Co-morbid Diagnoses: Reevaluate if insomnia persists after 7 to 10 days. (5.6)

6 ADVERSE REACTIONS

The most common adverse reactions (reported in ≥ 5% of patients treated with QUVIVIQ and at an incidence ≥ than placebo) were headache and somnolence or fatigue. (6.1)

To report SUSPECTED ADVERSE REACTIONS, contact Idorsia Pharmaceuticals Ltd at toll-free phone 1-833-400-9611 or FDA at 1-800-FDA-1088 or www.fda.gov/medwatch.

7 DRUG INTERACTIONS

- Strong CYP3A4 inhibitors: Avoid concomitant use. (2.2, 7.1)
- Moderate CYP3A4 inhibitors: Maximum recommended dose is 25 mg. (2.2, 7.1)
- Moderate or Strong CYP3A4 inducers: Avoid concomitant use. (7.1)

FULL PRESCRIBING INFORMATION

1 INDICATIONS AND USAGE

QUVIVIQ is indicated for the treatment of adult patients with insomnia, characterized by difficulties with sleep onset and/or sleep maintenance [see Clinical Studies (14.1)].

2 DOSAGE AND ADMINISTRATION

2.1 Recommended Dosage

The recommended dosage range is 25 mg to 50 mg of QUVIVIQ taken orally no more than once per night within 30 minutes of going to bed (with at least 7 hours remaining prior to planned awakening).

Time to sleep onset may be delayed if taken with or soon after a meal [see Clinical Pharmacology (12.3)].

2.2 Dosage Recommendations for Concomitant Use with CYP3A4 Inhibitors or CYP3A4 Inducers

Co-administration with Strong CYP3A4 Inhibitors

Avoid concomitant use of QUVIVIQ with strong inhibitors of CYP3A4 [see Drug Interactions (7.1), Clinical Pharmacology (12.3)].

Co-administration with Moderate CYP3A4 Inhibitors

The recommended dosage of QUVIVIQ is 25 mg no more than once per night when used with moderate inhibitors of CYP3A4 [see Drug Interactions (7.1), Clinical Pharmacology (12.3)].

Co-administration with Strong or Moderate CYP3A4 Inducers

Avoid concomitant use of QUVIVIQ with strong or moderate CYP3A4 inducers [see Drug Interactions (7.1)].

2.3 Dosage Recommendations for Patients with Hepatic Impairment

The maximum recommended dosage in patients with moderate hepatic impairment (Child-Pugh score 7–9) is 25 mg of QUVIVIQ no more than once per night [see Use in Specific Populations (8.6), Clinical Pharmacology (12.3)].

QUVIVIQ is not recommended in patients with severe hepatic impairment (Child-Pugh score ≥ 10) [see Use in Specific Populations (8.6)].

3 DOSAGE FORMS AND STRENGTHS

QUVIVIQ (daridorexant) tablets are available as:

25 mg: light purple, arc-triangle shaped, film-coated tablet debossed with "25" on one side and "i" (Idorsia logo) on the other side, containing 25 mg daridorexant.

50 mg: light orange, arc-triangle shaped, film-coated tablet debossed with "50" on one side and "i" (Idorsia logo) on the other side, containing 50 mg daridorexant.

4 CONTRAINDICATIONS

QUVIVIQ is contraindicated:

- in patients with narcolepsy.
- in patients with a history of hypersensitivity to daridorexant or any components of QUVIVIQ. Angioedema with pharyngeal involvement has been reported [see Adverse Reactions (6.2)].

5 WARNINGS AND PRECAUTIONS

5.1 CNS-Depressant Effects and Daytime Impairment

QUVIVIQ is a central nervous system (CNS) depressant that can impair daytime wakefulness even when used as prescribed. CNS-depressant effects may persist in some patients for up to several days after discontinuing QUVIVIQ. Prescribers should advise patients about the potential for next-day somnolence.

Driving ability was impaired in some subjects taking QUVIVIQ 50 mg [see Clinical Studies (14.2)]. The risk of daytime impairment is increased if QUVIVIQ is taken with less than a full night of sleep remaining or if a higher than recommended dose is taken [see Dosage and Administration (2.1)]. If QUVIVIQ is taken in these circumstances, caution patients against driving and other activities requiring complete mental alertness.

Co-administration with other CNS depressants (e.g., benzodiazepines, opioids, tricyclic antidepressants, alcohol) increases the risk of CNS depression, which can cause daytime impairment. Dosage adjustments of QUVIVIQ and of concomitant CNS depressants may be necessary when administered together because of potentially additive effects. The use of QUVIVIQ with other drugs to treat insomnia is not recommended. Advise patients not to consume alcohol in combination with QUVIVIQ because co-administration of QUVIVIQ with alcohol resulted in additive effects on psychomotor performance [see Drug Interactions (7.1)].

Because QUVIVIQ can cause drowsiness, patients, particularly the elderly, are at a higher risk of falls.

5.2 Worsening of Depression/Suicidal Ideation

Patients with psychiatric disorders, including insomnia, are at increased risk of suicide. In primarily depressed patients treated with hypnotics, worsening of depression and suicidal thoughts and actions (including completed suicides) have been reported. As with other hypnotics, QUVIVIQ should be administered with caution in patients exhibiting symptoms of depression. Monitoring of suicide risk and protective measures may be required.

5.3 Sleep Paralysis, Hypnagogic/Hypnopompic Hallucinations, and Cataplexy-like Symptoms

Sleep paralysis, an inability to move or speak for up to several minutes during sleep-wake transitions, and hypnagogic/hypnopompic hallucinations, including vivid and disturbing perceptions, can occur with the use of QUVIVIQ [see Adverse Reactions (6.1)]. Prescribers should explain the nature of these events to patients when prescribing QUVIVIQ.

Symptoms similar to mild cataplexy have been reported with orexin receptor antagonists. Such symptoms can include periods of leg weakness lasting from seconds to a few minutes, can occur either at night or during the day, and may not be associated with an identified triggering event (e.g., laughter or surprise).

5.4 Complex Sleep Behaviors

Complex sleep behaviors, including sleepwalking, sleep driving, and engaging in other activities while not fully awake (e.g., preparing and eating food, making phone calls, having sex), have been reported to occur with the use of hypnotics, including orexin receptor antagonists such as QUVIVIQ. These events can occur in hypnotic-naïve as well as in hypnotic-experienced persons. Patients usually do not remember these events. Complex sleep behaviors may occur following the first or any subsequent use of hypnotics, such as QUVIVIQ, with or without the concomitant use of alcohol and other CNS depressants [see Drug Interactions (7.1)]. Discontinue QUVIVIQ immediately if a patient experiences a complex sleep behavior.

5.5 Patients with Compromised Respiratory Function

QUVIVIQ has been studied in mild to severe OSA not using CPAP, and in patients with moderate COPD. The effects of QUVIVIQ on respiratory function should be considered if prescribed to patients with compromised respiratory function. QUVIVIQ has not been studied in patients with mild or severe COPD [see Use in Specific Populations (8.7)].

5.6 Need to Evaluate for Co-morbid Diagnoses

Because sleep disturbances may be the presenting manifestation of a medical and/or psychiatric disorder, treatment of insomnia should be initiated only after careful evaluation of the patient. The failure of insomnia to remit after 7 to 10 days of treatment may indicate the presence of a primary psychiatric and/or medical illness that should be evaluated. Worsening of insomnia or the emergence of new cognitive or behavioral abnormalities may be the result of an unrecognized underlying psychiatric or medical disorder and can emerge during the course of treatment with sleep-promoting drugs such as QUVIVIQ.

6 ADVERSE REACTIONS

The following are discussed in detail in other sections of the labeling:

- CNS-Depressant Effects and Daytime Impairment [see Warnings and Precautions (5.1)]
- Worsening of Depression/Suicidal Ideation [see Warnings and Precautions (5.2)]
- Sleep Paralysis, Hypnagogic/Hypnopompic Hallucinations, and Cataplexy-like Symptoms [see Warnings and Precautions (5.3)]
- Complex Sleep Behaviors [see Warnings and Precautions (5.4)]
- Patients with Compromised Respiratory Function [see Warnings and Precautions (5.5)]

6.1 Clinical Trials Experience

Because clinical trials are conducted under widely varying conditions, adverse reaction rates observed in clinical trials of a drug cannot be directly compared to rates in clinical trials of another drug and may not reflect the rates observed in practice.

The safety of QUVIVIQ was evaluated in three placebo-controlled clinical studies (two 3-month studies of identical design [Study 1 and Study 2], and a 9-month extension study [Study 3]). Study 1 evaluated 50 mg and 25 mg doses of QUVIVIQ, while Study 2 evaluated a 25 mg dose and a 10 mg dose of QUVIVIQ. The 10 mg dose is not an approved dose. A total of 1232 patients (including approximately 40% elderly patients [≥ 65 years old]), received QUVIVIQ 50 mg (N = 308); 25 mg (N = 618); or 10 mg (an unapproved dose) (N = 306). A total of 576 patients were treated with QUVIVIQ for at least 6 months and 331 for at least 12 months.

Most Common Adverse Reactions

The most common reported adverse reaction (in at least 5% of patients and greater than placebo) during double-blind treatment in Study 1 was headache.

Table 1 shows adverse reactions that occurred in at least 2% of patients treated with QUVIVIQ and more frequently than in patients who received placebo in Study 1.

Table 1 Adverse Reactions Reported in ≥ 2% of QUVIVIQ-treated Patients and Greater than in Placebo-treated Patients in a 3-Month Placebo-Controlled Study (Study 1)
 | QUVIVIQ | QUVIVIQ | Placebo
 | 25 mg | 50 mg
 | (N=310) | (N=308) | (N=309)
 | % | % | %
Nervous System Disorders
Headache [The following terms were combined: Headache includes: headache, tension headache, migraine, migraine with aura, head discomfort Somnolence or fatigue includes: somnolence, sedation, fatigue, hypersomnia, lethargy Dizziness includes: dizziness, vertigo, labyrinthitis Nausea includes: nausea, vomiting, procedural nausea] | 6 | 7 | 5
Somnolence or fatigue | 6 | 5 | 4
Dizziness | 2 | 3 | 2
Gastro-intestinal disorders
Nausea | 0 | 3 | 2

Other Adverse Reactions Observed During Clinical Trials (Study 1 and Study 2)

Other adverse reactions of < 2% frequency but greater than placebo are shown below. The following do not include adverse reactions 1) for which a drug cause was remote, 2) that were so general as to be uninformative, or 3) that were not considered to have clinically significant implications.

- Sleep paralysis was reported in 0.5% and 0.3% of patients receiving QUVIVIQ 25 mg and 50 mg, respectively, compared to no reports for placebo.
- Hypnagogic and hypnopompic hallucinations were reported in 0.6% of patients receiving QUVIVIQ 25 mg compared to no cases with QUVIVIQ 50 mg or placebo.

6.2 Post-Marketing Experience

The following adverse reactions have been identified during post-approval use of QUVIVIQ. Because these reactions are reported voluntarily from a population of uncertain size, it is not always possible to reliably estimate their frequency or establish a causal relationship to drug exposure.

Psychiatric disorders: Nightmares or abnormal dreams

Immune system disorders: Hypersensitivity (including angioedema, rash, urticaria)

7 DRUG INTERACTIONS

7.1 Effects of Other Drugs on QUVIVIQ

Table 2 describes clinically significant drug interactions where the concomitant use of other drugs affects QUVIVIQ.

Table 2 Effects of Other Drugs on QUVIVIQ
Strong or Moderate CYP3A4 Inhibitors
Clinical Implications: | Concomitant use with a strong or moderate CYP3A4 inhibitor increases exposure to daridorexant [see Clinical Pharmacology (12.3)], which may increase the risk of QUVIVIQ adverse reactions.
Prevention or Management: | The recommended dose of QUVIVIQ is 25 mg when used with a moderate CYP3A4 inhibitor [see Dosage and Administration (2.2)]. Concomitant use of QUVIVIQ with a strong inhibitor of CYP3A4 is not recommended [see Dosage and Administration (2.2)].
Strong and Moderate CYP3A4 Inducers
Clinical Implications: | Concomitant use with a strong or moderate CYP3A4 inducer decreases exposure to daridorexant [see Clinical Pharmacology (12.3)], which may reduce the efficacy of QUVIVIQ.
Prevention or Management: | Concomitant use of QUVIVIQ with a strong or moderate inducer of CYP3A4 is not recommended [see Dosage and Administration (2.2)].
Alcohol and Other CNS Depressants
Clinical Implications: | Concomitant use of alcohol or other CNS depressants with QUVIVIQ may lead to additive impairment of psychomotor performance and risk of CNS depression [see Clinical Pharmacology (12.2)].
Prevention or Management: | Avoid alcohol consumption with QUVIVIQ [see Warnings and Precautions (5.1)]. Use with caution in patients receiving CNS depressants. Consider dose adjustment of QUVIVIQ and/or the CNS depressant(s) if used concomitantly [see Warnings and Precautions (5.1)].

7.2 Effects of QUVIVIQ on Other Drugs

Table 3 describes clinically significant drug interactions where the concomitant use of QUVIVIQ affects other drugs.

Table 3 Effects of QUVIVIQ on Other Drugs
CYP3A4 Substrates
Clinical Implications: | Concomitant use of QUVIVIQ with CYP3A4 substrates increases the exposure to CYP3A4 substrate [see Clinical Pharmacology (12.3)].
Prevention or Management: | Use with caution in patients receiving CYP3A4 substrates with narrow therapeutic index.
P-gp Substrates
Clinical Implications: | Concomitant use of QUVIVIQ with P-gp substrates increases the exposure to P-gp substrate [see Clinical Pharmacology (12.3)].
Prevention or Management: | Use with caution in patients receiving P-gp substrates with a narrow therapeutic index.

8 USE IN SPECIFIC POPULATIONS

8.1 Pregnancy

Pregnancy Exposure Registry

There will be a pregnancy exposure registry that monitors pregnancy outcomes in women exposed to QUVIVIQ during pregnancy. Pregnant women exposed to QUVIVIQ and healthcare providers are encouraged to call Idorsia Pharmaceuticals Ltd at 1-833-400-9611.

Risk Summary

There are no available data on QUVIVIQ use in pregnant women to evaluate for drug-associated risks of major birth defects, miscarriage, or other adverse maternal or fetal outcomes. In animal reproduction studies, oral administration of daridorexant to pregnant rats and rabbits during the period of organogenesis did not cause fetal toxicity or malformation at doses up to 8 and 10 times the maximum recommended human dose (MRHD) of 50 mg, respectively, based on AUC. Oral administration of daridorexant to pregnant and lactating rats did not cause any maternal or developmental toxicity at doses up to 9 times the MRHD, based on AUC (see Data).

The estimated background risk of major birth defects and miscarriage for the indicated population is unknown. All pregnancies have a background risk of birth defect, loss, or other adverse outcomes. In the U.S. general population, the estimated background risk of major birth defects and miscarriage in clinically recognized pregnancies is 2% to 4% and 15% to 20%, respectively.

Data

Animal Data

Daridorexant was administered orally to pregnant rats during the period of organogenesis at doses of 30, 100, and 300 mg/kg/day, which are approximately 1, 3, and 8 times the MRHD of 50 mg, respectively, based on AUC. Daridorexant did not cause any maternal or embryofetal toxicities or fetal malformation at doses up to 300 mg/kg/day. The NOAEL for maternal and fetal toxicity is 300 mg/kg/day, which is approximately 8 times the MRHD of 50 mg, based on AUC.

Daridorexant was administered orally to pregnant rabbits during the period of organogenesis at doses of 30, 60, and 120 mg/kg/day, which are approximately 3, 4, and 10 times the MRHD of 50 mg, respectively, based on AUC. Daridorexant did not cause any fetal toxicity or malformation at doses up to 120 mg/kg/day. Daridorexant caused maternal toxicities of decreased weight gain and food consumption at the dose of 120 mg/kg/day. The NOAELs for maternal and fetal toxicity are 60 and 120 mg/kg/day, respectively, which are approximately 4 and 10 times the MRHD of 50 mg, respectively, based on AUC.

Daridorexant was administered orally to pregnant rats during gestation and lactation at doses of 50, 100, and 300 mg/kg/day, which are approximately 1, 3, and 9 times the MRHD of 50 mg, respectively, based on AUC. Daridorexant did not cause any maternal or developmental toxicities at doses up to 300 mg/kg/day. The NOAEL for maternal and developmental toxicity is 300 mg/kg/day, which is approximately 9 times the MRHD of 50 mg, based on AUC.

8.2 Lactation

Risk Summary

Daridorexant is present in human breast milk in low amounts. In a clinical lactation study, daridorexant was detected in human milk at a mean daily infant dose of 0.0016 mg/kg, with a relative infant dose of <1% the maternal weight-adjusted dose (see Data). There are no data on the effects of daridorexant on the breastfed infant or its effects on milk production.

Infants exposed to QUVIVIQ through breastmilk should be monitored for excessive sedation. The developmental and health benefits of breastfeeding should be considered along with the mother's clinical need for QUVIVIQ and any potential adverse effects on the breastfed infant from QUVIVIQ or from the underlying maternal condition.

Data

A lactation study in 10 healthy adult lactating women evaluated the concentrations of daridorexant in plasma and breast milk following a single dose of 50 mg daridorexant. The calculated mean daily infant dose is 0.0016 mg/kg based on an assumed infant body weight of 6 kg, and the relative infant dose is 0.22% of the maternal weight-adjusted dose. Approximately 87% of the total amount of daridorexant present in milk was detected by 24 hours after administration. The amount of daridorexant present in breast milk at steady state is expected to be similar to that after a single dose.

8.4 Pediatric Use

The safety and effectiveness of QUVIVIQ have not been established in pediatric patients.

8.5 Geriatric Use

No dose adjustment is required in patients over the age of 65 years.

Of the total number of subjects in the clinical studies of QUVIVIQ with insomnia (N = 1854), approximately 39% (N = 727) were ≥ 65 years and 5.9% (N = 110) were ≥ 75 years. The likelihood of somnolence and fatigue increased with patient age.

Because QUVIVIQ can increase somnolence and drowsiness, patients, particularly the elderly, are at higher risk of falls [see Warnings and Precautions (5.1)].

8.6 Hepatic Impairment

QUVIVIQ has not been studied in patients with severe hepatic impairment (Child-Pugh score ≥ 10). Use in this population is not recommended [see Clinical Pharmacology (12.3)].

Reduce the dose of QUVIVIQ in patients with moderate hepatic impairment (Child-Pugh score 7–9) [see Dosage and Administration (2.3)]. Moderate hepatic impairment may increase daridorexant systemic exposure to a clinically relevant extent [see Clinical Pharmacology (12.3)], which may increase the frequency or severity of adverse reactions.

8.7 Patients with Compromised Respiratory Function

Obstructive Sleep Apnea

The respiratory depressant effect of QUVIVIQ was evaluated after one night and after five consecutive nights of treatment with QUVIVIQ 50 mg in a randomized, placebo-controlled, two-period crossover study in 25 patients with mild to moderate OSA (apnea-hypopnea index [AHI] 5 to 30 events per hour of sleep) not using CPAP. Following once-daily dosing of 50 mg in the evening, the mean treatment difference (daridorexant – placebo) on Day 5 for AHI was 0.74 (90% CI, -1.43 to 2.92).

QUVIVIQ was also evaluated after 5 consecutive nights of treatment with QUVIVIQ 50 mg in a randomized, placebo-controlled, double-blind, two-period crossover study in 16 patients with severe OSA (apnea-hypopnea index ≥ 30 events per hour of sleep; studied range 30.8–82.2 events per hour) not using CPAP. Following once daily dosing of 50 mg in the evening, the mean treatment difference (daridorexant – placebo) on Day 5 for AHI was -3.74 (90% CI, -11.71 to 4.23).

Due to study limitations, including the short duration of the studies, clinically meaningful respiratory effects of QUVIVIQ in OSA cannot be excluded, including for long-term treatment [see Warnings and Precautions (5.5)].

Chronic Obstructive Pulmonary Disease

The respiratory depressant effect of QUVIVIQ was evaluated after one night and after five consecutive nights of treatment with QUVIVIQ 50 mg in a randomized, placebo-controlled, two-period crossover study in 25 patients with moderate COPD (FEV1/FVC ratio ≤ 70% and 40% ≤ FEV1 < 80% of predicted). Following once-daily dosing of 50 mg in the evening, the mean SpO2 treatment difference (daridorexant – placebo) on Day 5 was 0.18% (90% CI, -0.21 to 0.57).

QUVIVIQ has not been studied in patients with mild (FEV1 ≥ 80% predicted) or severe COPD (FEV1 < 40% of predicted).

Clinically meaningful respiratory effects of QUVIVIQ in patients with compromised respiratory function cannot be excluded [see Warnings and Precautions (5.5)].

9 DRUG ABUSE AND DEPENDENCE

9.1 Controlled Substance

QUVIVIQ contains daridorexant, a Schedule IV controlled substance.

9.2 Abuse

Drug abuse is the intentional, non-therapeutic use of a drug, even once, for its desirable psychological or physiological effects. The abuse potential of daridorexant was evaluated in preclinical models, recreational sedative drug users, and insomnia subjects.

In a human abuse potential study conducted in 63 recreational sedative drug users, the effect of single-dose administration of QUVIVIQ [50 mg, 100 mg (two times the maximum recommended dose), and 150 mg (three times the maximum recommended dose)], zolpidem (30 mg), suvorexant (150 mg), and placebo on subjective rating of "drug liking" was evaluated. At the dose of 50 mg, QUVIVIQ showed significantly lower "drug liking" ratings than zolpidem (30 mg) and suvorexant (150 mg), but significantly higher than placebo. At doses of 100 mg (two times the maximum recommended dose) and 150 mg (three times the maximum recommended dose), QUVIVIQ showed similar "drug liking" ratings to zolpidem (30 mg) and suvorexant (150 mg).

In placebo-controlled Phase 3 clinical studies in which 1232 subjects with insomnia were treated with QUVIVIQ for up to 12 months, there were no reports indicative of abuse liability. Because individuals with a history of abuse of or addiction to alcohol or other drugs may be at increased risk for abuse of or addiction to QUVIVIQ, follow such patients carefully.

9.3 Dependence

Physical dependence is a state that develops as a result of physiological adaptation in response to repeated drug use, manifested by withdrawal signs and symptoms upon abrupt treatment discontinuation or a significant dose reduction of a drug.

In animal studies and clinical trials evaluating physical dependence, chronic administration of daridorexant did not produce withdrawal signs or symptoms upon drug discontinuation. This suggests that daridorexant does not produce physical dependence.

10 OVERDOSAGE

There is limited clinical experience with QUVIVIQ overdose. In clinical pharmacology studies, healthy subjects were administered single doses of up to 200 mg (4 times the maximum recommended dose) of QUVIVIQ. The following adverse reactions were observed: somnolence, muscle weakness, cataplexy-like symptoms, sleep paralysis, disturbance in attention, fatigue, headache, and constipation.

There is no specific antidote to an overdosage of QUVIVIQ. In the event of an overdose, general symptomatic and supportive medical care, along with immediate gastric lavage where appropriate, should be provided and patients should be carefully monitored. Dialysis is unlikely to be effective as daridorexant is highly protein bound. Consider contacting the Poison Help Line (1-800-222-1222) or a medical toxicologist for additional overdosage management recommendations.

11 DESCRIPTION

QUVIVIQ contains daridorexant, an orexin receptor antagonist, present as daridorexant hydrochloride salt. The chemical name of daridorexant hydrochloride is (S)-(2-(5-chloro-4-methyl-1H-benzo[d]imidazol-2-yl)-2-methylpyrrolidin-1-yl)(5-methoxy-2-(2H-1,2,3-triazol-2-yl)phenyl)methanone hydrochloride. The molecular formula is C23H23N6O2Cl * HCl. The molecular weight is 487.38 g/mol.

The structural formula is:

Daridorexant hydrochloride is a white to light yellowish powder that is very slightly soluble in water.

QUVIVIQ tablets are intended for oral administration. Each film-coated tablet contains daridorexant 25 mg or 50 mg, equivalent to 27 mg or 54 mg of daridorexant hydrochloride, respectively. The inactive ingredients are croscarmellose sodium, magnesium stearate, mannitol, microcrystalline cellulose, povidone, and silicon dioxide.

In addition, the film coating contains the following inactive ingredients: glycerin, hypromellose, iron oxide black, iron oxide red, microcrystalline cellulose, talc, titanium dioxide, and, in the 50 mg tablet only, iron oxide yellow.

12 CLINICAL PHARMACOLOGY

12.1 Mechanism of Action

The mechanism of action of daridorexant in the treatment of insomnia is presumed to be through antagonism of orexin receptors. The orexin neuropeptide signaling system plays a role in wakefulness. Blocking the binding of wake-promoting neuropeptides orexin A and orexin B to receptors OX1R and OX2R is thought to suppress wake drive.

12.2 Pharmacodynamics

Daridorexant binds to and inhibits the orexin receptors OX1R and OX2R (Ki = 0.47 and 0.93 nM, respectively).

Cardiac Electrophysiology

At a dose 4 times the maximum recommended dose, QUVIVIQ does not prolong the QTc interval to any clinically relevant extent.

Alcohol

Co-administration of a single 50 mg dose of QUVIVIQ with alcohol at a blood level of 0.6 g/L led to additive effects on impairment of psychomotor performance (postural stability and alertness). Daridorexant did not affect alcohol concentrations and alcohol did not affect daridorexant concentrations [see Warnings and Precautions (5.1, 5.4), Drug Interactions (7.1)].

Citalopram

No clinically significant effect on psychomotor performance was observed when 50 mg QUVIVIQ was co-administered with 20 mg citalopram in healthy subjects at steady state.

12.3 Pharmacokinetics

Daridorexant plasma exposure is dose proportional from 25 mg to 50 mg. The daridorexant pharmacokinetic profile is similar following multiple-dose and single-dose administration with no accumulation.

Absorption

Daridorexant reaches peak plasma concentrations within 1–2 hours (Tmax). Daridorexant has an absolute bioavailability of 62%.

Effect of food

In healthy subjects, a high-fat and high-calorie meal delayed the Tmax by 1.3 hours and decreased the Cmax by 16%, but did not affect the total exposure (AUC).

Distribution

Daridorexant has a volume of distribution of 31 L. Daridorexant is 99.7% bound to plasma proteins. The blood to plasma ratio is 0.64.

Elimination

The terminal half-life of daridorexant is approximately 8 hours.

Metabolism

Daridorexant undergoes extensive metabolism and is primarily metabolized by CYP3A4 (89%). Other CYP enzymes individually contribute to less than 3% of metabolic clearance of daridorexant.

Excretion

The primary route of daridorexant excretion is via feces (approximately 57%), followed by urine (approximately 28%), primarily as metabolites. Trace amounts of parent drug were found in feces and urine.

Specific Populations

Age, sex, race (White, Black, Asian), body size, and mild to severe renal impairment (Cockcroft-Gault < 30 mL/min, not on dialysis) did not have a clinically significant effect on the pharmacokinetics of daridorexant. The effect of severe hepatic impairment (Child-Pugh score ≥ 10) on the pharmacokinetics of daridorexant has not been studied.

Effects of hepatic impairment and renal impairment on the exposure to daridorexant are summarized in Figure 1.

Figure 1 Effects of hepatic impairment and renal impairment on daridorexant PK

Daridorexant dose: 25 mg. Data are GMRs and 90% CIs. Hepatic impairment PK variables are based on the unbound fraction of daridorexant. Reference = matched healthy subjects. AUC = area under the plasma concentration-time curve from zero to infinity; CI = confidence interval; Cmax = maximum plasma concentration; GMR = geometric mean ratio; PK = pharmacokinetics.

Drug Interaction Studies

The effects of other compounds on the exposure to daridorexant are summarized in Figure 2. The effects of daridorexant on the exposure to other compounds are summarized in Figure 3.

Effect of Other Compounds on QUVIVIQ

Figure 2 Effect of co-administered compounds on the PK of daridorexant

Daridorexant 50 mg was administered with interacting drugs, except with diltiazem (25 mg daridorexant). Interacting drugs were administered in multiple-dose fashion, except famotidine (single dose) and alcohol (5 h infusion at 0.6 g/L). Based on PBPK analysis: Concomitant use of itraconazole (a strong CYP3A4 inhibitor) increased daridorexant AUC by more than 400%. Concomitant use of rifampin (a strong CYP3A4 inducer) decreased daridorexant AUC by more than 50%. Data are GMRs and 90% CIs. Some 90% CIs are too narrow to be shown. AUC = area under the plasma concentration-time curve; CI = confidence interval; Cmax = maximum plasma concentration; GMR = geometric mean ratio; SSRI = selective serotonin reuptake inhibitor.

Effect of QUVIVIQ on Other Compounds

Figure 3 Effect of daridorexant on the PK of other compounds

AUC = area under the plasma concentration-time curve; BCRP = breast cancer resistance protein; CI = confidence interval; Cmax = maximum plasma concentration; CP = cytochrome P450 enzyme; P-gp = P-glycoprotein; SSRI = selective serotonin reuptake inhibitor.

13 NONCLINICAL TOXICOLOGY

13.1 Carcinogenesis, Mutagenesis, Impairment of Fertility

Carcinogenesis

Daridorexant did not increase the incidence of tumors in rats treated for 2 years at oral doses of 15, 50, and 150 mg/kg/day. The high dose of 150 mg/kg/day is approximately 4 times the MRHD of 50 mg, based on AUC. Daridorexant did not increase the incidence of tumors in Tg.rasH2 mice treated for 26 weeks at oral doses of 100, 300, and 1000 mg/kg/day in males or 100, 200, and 1000 mg/kg/day in females.

Mutagenesis

Daridorexant was not mutagenic in the in vitro bacterial reverse mutation (Ames) assay or in the in vitro mammalian chromosome aberration assay in human lymphocytes and was not clastogenic in the in vivo rat micronucleus assay.

Impairment of Fertility

Daridorexant was orally administered to female rats at doses of 30, 100, and 300 mg/kg/day prior to and throughout mating and continuing to gestation Day 6. These doses are approximately 0.5, 3, and 9 times the MRHD of 50 mg, based on AUC. Daridorexant increased pre-implantation loss and decreased implantation sites without affecting mating or fertility at 300 mg/kg/day. The NOAEL for female fertility is 100 mg/kg/day, which is approximately 3 times the MRHD of 50 mg, based on AUC.

Daridorexant did not affect fertility when orally administered to male rats at doses of 50, 150, and 450 mg/kg/day prior to and throughout mating. These doses are approximately 1, 3, and 7 times the MRHD of 50 mg, based on AUC.

13.2 Animal Toxicology and/or Pharmacology

In dogs, daily oral administration of daridorexant at ≥ 30 mg/kg/day resulted in behavior characteristic of cataplexy when presented with positive stimulation. The no-observed-effect level (NOEL) for cataplexy is 20 mg/kg/day, which is approximately 3 times the MRHD of 50 mg, based on Cmax and AUC.

14 CLINICAL STUDIES

14.1 Controlled Clinical Studies

The efficacy of QUVIVIQ was evaluated in two multicenter, randomized, double-blind, placebo-controlled, parallel-group studies, Study 1 (NCT03545191) and Study 2 (NCT03575104).

A total of 1854 patients with Diagnostic and Statistical Manual of Mental Disorders, 5th edition (DSM-5®) insomnia were randomized to receive QUVIVIQ or placebo once daily, in the evening, for 3 months. Study 1 randomized 930 subjects to QUVIVIQ 50 mg (N = 310), 25 mg (N = 310) or placebo (N = 310). Study 2 randomized 924 subjects to QUVIVIQ 25 mg (N = 309), 10 mg (N = 307), or placebo (N = 308). The 10 mg dose is not an approved dose.

At the end of the 3-month treatment period, both studies included a 7-day placebo run-out period, after which patients could enter a 9-month, double-blind, placebo-controlled extension study (Study 3, NCT03679884).

In Study 1, patients had a mean age of 55.4 years (range 18 to 88 years), with 39.1% of subjects ≥ 65 years of age, including 5.8% ≥ 75 years of age. Patients were identified as female or male and by US census-based racial and ethnic categories. The percentages of patients in the respective categories were: female sex (67.1%), White (90%), Black or African American (8%), Asian (1.0%), or Other race (< 1%).

In Study 2, patients had a mean age of 56.7 years (range 19 to 85 years), with 39.3% of subjects ≥ 65 years of age, including 6.1% ≥ 75 years of age. Patients were identified as female or male and by US census-based racial and ethnic categories. The percentages of patients in the respective categories were: female sex (69.0%), White (88%), Black or African American (8%), Asian (4%), or Other race (< 1%).

Primary efficacy endpoints for both studies were the change from baseline to Month 1 and Month 3 in Latency to Persistent Sleep (LPS) and Wake After Sleep Onset (WASO), measured objectively by polysomnography in a sleep laboratory. LPS is a measure of sleep induction and WASO is a measure of sleep maintenance.

Secondary endpoint included in the statistical testing hierarchy with Type 1 error control was patient-reported Total Sleep Time (sTST), evaluated every morning at home using a validated Sleep Diary Questionnaire (SDQ).

In Study 1, doses of 25 and 50 mg QUVIVIQ showed a statistically significant improvement vs placebo on polysomnography (LPS, WASO) and self-reported total sleep (sTST), at Month 1 and Month 3 (Table 4).

In Study 2, QUVIVIQ 25 mg showed a statistically significant improvement vs placebo on WASO and sTST at Month 1 and Month 3 (Table 5). QUVIVIQ 10 mg did not show a statistically significant improvement on LPS, WASO, or sTST at Month 1 or Month 3.

The efficacy of QUVIVIQ was similar across subgroups based on age, sex, race, and region.

Table 4 Primary and Secondary Efficacy Results for Change from Baseline in Sleep Onset, Sleep Maintenance, and Subjective Total Sleep Time at Month 1 and Month 3 in Patients with Insomnia (Study 1)
Treatment group/dose (N) | Baseline | Month 1 |  |  | Month 3
Treatment group/dose (N) |  |  | Change from baseline | Difference to placebo |  | Change from baseline | Difference to placebo
 | mean (SD) | mean (SD) | LSM (95%CL) | LSM (95%CL) | mean (SD) | LSM (95%CL) | LSM (95%CL)
WASO (wake after sleep onset, min): sleep maintenance, assessed by PSG
50 mg (310) | 95 (38) | 65 (35) | -29 [-33, -25] | -23 [doses that were statistically significantly superior (p < 0.05) to placebo after controlling for multiple comparisons.] [-28, -18] | 65 (39) | -29 [-33, -25] | -18 [-24, -13]
25 mg (310) | 98 (39) | 77 (42) | -18 [-22, -15] | -12 [-17, -7] | 73 (40) | -23 [-27, -19] | -12 [-17, -6]
placebo (310) | 103 (41) | 92 (42) | -6 [-10, -2] |  | 87 (43) | -11 [-15, -7]
LPS (latency to persistent sleep, min): sleep onset, assessed by PSG
50 mg (310) | 64 (37) | 34 (27) | -31 [-35, -28] | -11 [-16, -7] | 30 (23) | -35 [-38, -31] | -12 [-16, -7]
25 mg (310) | 67 (39) | 38 (32) | -28 [-32, -25] | -8 [-13, -4] | 36 (34) | -31 [-34, -27] | -8 [-12, -3]
placebo (310) | 67 (40) | 46 (36) | -20 [-23, -17] |  | 43 (34) | -23 [-26, -20]
sTST (subjective total sleep time, min): patient-reported
50 mg (310) | 313 (58) | 358 (74) | 44 [38, 49] | 22 [14, 30] | 372 (79) | 58 [51, 64] | 20 [11, 29]
25 mg (310) | 310 (60) | 345 (66) | 34 [29, 40] | 13 [5, 20] | 358 (72) | 48 [41, 54] | 10 [1, 19]
placebo (310) | 316 (53) | 338 (65) | 22 [16, 27] |  | 354 (73) | 38 [31, 44]
CL = confidence limit; LPS = latency to persistent sleep; LSM = least squares mean; PSG = polysomnography; SD = standard deviation; sTST = subjective total sleep time; WASO = wake after sleep onset.

Table 5 Primary and Secondary Efficacy Results for Change from Baseline in Sleep Onset, Sleep Maintenance, and Subjective Total Sleep Time at Month 1 and Month 3 in Patients with Insomnia (Study 2)
Treatment group/dose (N) | Baseline | Month 1 |  |  | Month 3
Treatment group/dose (N) |  |  | Change from baseline | Difference to placebo |  | Change from baseline | Difference to placebo
 | mean (SD) | mean (SD) | LSM (95%CL) | LSM (95%CL) | mean (SD) | LSM (95%CL) | LSM (95%CL)
WASO (wake after sleep onset, min): sleep maintenance, assessed by PSG
25 mg (309) | 106 (49) | 80 (44) | -24 [-28, -20] | -12 [doses that were statistically significantly superior (p < 0.05) to placebo after controlling for multiple comparisons.] [-18, -6] | 80 (49) | -24 [-29, -19] | -10 [-17, -4]
placebo (308) | 108 (49) | 93 (50) | -13 [-17, -8] |  | 91 (47) | -14 [-19, -9]
LPS (latency to persistent sleep, min): sleep onset, assessed by PSG
25 mg (309) | 69 (41) | 42 (39) | -26 [-31, -22] | -6 [-12, -1] | 39 (37) | -29 [-33, -24] | -9 [-15, -3]
placebo (308) | 72 (46) | 50 (40) | -20 [-24, -16] |  | 49 (46) | -20 [-24, -15]
sTST (subjective total sleep time, min): patient-reported
25 mg (309) | 308 (53) | 353 (67) | 44 [38, 49] | 16 [8, 24] | 365 (70) | 56 [50, 63] | 19 [10, 28]
placebo (308) | 308 (52) | 336 (63) | 28 [22, 33] |  | 347 (65) | 37 [31, 43]
CL = confidence limit; LPS = latency to persistent sleep; LSM = least squares mean; PSG = polysomnography; SD = standard deviation; sTST = subjective total sleep time; WASO = wake after sleep onset.

The effects of QUVIVIQ on LPS, WASO, and sTST were observed at Month 1 and were maintained through Month 3. The change from baseline of sTST by week in Study 1 is presented in Figure 4.

Figure 4 Change from Baseline of sTST by Week (Study 1)

14.2 Special Safety Studies

Effects on Driving

A randomized, double-blind, placebo- and active-controlled, four-period crossover study evaluated the effects of nighttime administration of QUVIVIQ on next-morning driving performance, using a driving simulator, 9 hours after dosing in 30 healthy elderly subjects (65–79 years, median age 70 years; 15 men, 15 women) and 30 healthy adult subjects (50–64 years, median age 58 years; 15 men, 15 women). The primary driving performance outcome measure was change in Standard Deviation of Lateral Position (SDLP). Testing was conducted after one night (initial dosing) and after four consecutive nights of treatment with QUVIVIQ 50 mg and 100 mg (two times the maximum recommended daily dose). Zopiclone 7.5 mg was used as an active comparator. For both doses, QUVIVIQ caused a statistically significant impairment in next-morning driving performance in adult or elderly subjects (compared with placebo) after the first dose. Although the mean effect on driving performance was not statistically significant (compared to placebo) after 4 consecutive nights of treatment with either dose of QUVIVIQ, driving ability was impaired in some subjects taking QUVIVIQ.

Patients should be cautioned about the potential for next-morning driving impairment because there is individual variation in sensitivity to QUVIVIQ.

Withdrawal of Therapy

Withdrawal Symptoms

In controlled efficacy and safety studies, withdrawal effects were assessed by the Tyrer Benzodiazepine Withdrawal Symptom Questionnaire following discontinuation of QUVIVIQ, and by adverse event reporting during a single-blind placebo run-out period. No evidence of withdrawal symptoms was observed upon treatment discontinuation.

Loss of Treatment Effect After Discontinuation

The loss of effect from stopping treatment with QUVIVIQ was assessed during the placebo run-out period after 3 months of treatment with QUVIVIQ in Study 1 and Study 2.

After treatment discontinuation, in Study 1, patients previously treated with QUVIVIQ 50 mg experienced mean increases of 25 minutes in WASO, 16 minutes in LPS during the next night of sleep, and a mean decrease in sTST of 14 minutes per night over the next week, as compared to the last assessment on treatment. Following QUVIVIQ 25 mg discontinuation, a similar pattern was observed with mean increases in WASO of 19 minutes, 15 minutes in LPS, and a mean decrease in sTST of 7 minutes. Similar changes were observed with the 25 mg dose in Study 2. In both studies, patients who were on placebo and continued on placebo in the run-out period experienced minimal changes in WASO, LPS, or sTST.

Middle of the Night Safety

The effect of QUVIVIQ on middle of the night safety was evaluated in a randomized, placebo-controlled three-period crossover study in 18 healthy adult (< 65 years) and 18 healthy elderly (≥ 65 years) subjects. The ability to awaken in response to a sound stimulus, postural stability, and memory were assessed following a scheduled awakening 4 hours after administration of 25 or 50 mg QUVIVIQ, or placebo.

The ability to awaken to sound in the middle of the night was assessed using an audiometer that delivered 1000 Hz tones starting at 35 dB and increasing to 100 dB to determine the Auditory Awakening Threshold (AAT). There was no significant difference between QUVIVIQ (25 mg or 50 mg) and placebo in AAT.

Postural stability was measured by assessing body sway using a body sway meter approximately 5 minutes after awakening. Evening dosing of QUVIVIQ 25 mg and 50 mg resulted in respective increases in mean (95% confidence limit) cumulative body sway over 2 minutes of 37 mm [2 mm, 71 mm] and 66 mm [31 mm, 100 mm] at 4 hours post-dose compared to placebo.

A visual verbal learning test (VVLT) of immediate and delayed recall was administered to assess memory after middle of the night awakening (4 hours post-dose) in subjects receiving QUVIVIQ 25 mg or 50 mg. QUVIVIQ was associated with worse performance on the VVLT compared to placebo.

16 HOW SUPPLIED/STORAGE AND HANDLING

16.1 How Supplied

QUVIVIQ tablets are available as:

- 25 mg, light purple, arc-triangle shaped film-coated tablets debossed with "25" on one side, and "i" on the other side.
  NDC 80491-7825-3, bottle of 30 with child-resistant closure
- 50 mg: light orange, arc-triangle shaped film-coated tablets debossed with "50" on one side, and "i" on the other side.
  NDC 80491-7850-3, bottle of 30 with child-resistant closure

16.2 Storage and Handling

Store at 20°C to 25°C (68°F to 77°F), excursions permitted between 15°C and 30°C (59°F and 86°F) [see USP Controlled Room Temperature].

17 PATIENT COUNSELING INFORMATION

Advise the patient to read the FDA-approved patient labeling (Medication Guide).

Administration Instructions

Advise patients to take QUVIVIQ only in the evening within 30 minutes before going to bed and only if they can stay in bed for a full night (at least 7 hours) before being active again [see Dosage and Administration (2.1)].

Advise patients that the effect of QUVIVIQ may be delayed if taken with or soon after a meal [see Dosage and Administration (2.1), Clinical Pharmacology (12.3)].

CNS-Depressant Effects and Daytime Impairment

Advise patients that QUVIVIQ can impair daytime wakefulness even when used as prescribed. The risk of daytime impairment is increased if QUVIVIQ is taken with less than a full night of sleep remaining or if a higher than recommended dose is taken. If QUVIVIQ is taken in these circumstances, caution patients against driving and other activities requiring complete mental alertness. Advise patients that increased drowsiness may increase the risk of falls in some patients [see Warnings and Precautions (5.1), Clinical Studies (14.2)].

Worsening of Depression/Suicidal Ideation

Tell patients to report any worsening of depression or suicidal thoughts immediately [see Warnings and Precautions (5.2)].

Sleep Paralysis, Hypnagogic/Hypnopompic Hallucinations, and Cataplexy-Like Symptoms

Advise patients and their families that QUVIVIQ may cause sleep paralysis, which is an inability to move or speak for several minutes during sleep-wake transitions and hypnagogic/hypnopompic hallucinations, including vivid and disturbing perceptions. Symptoms similar to mild cataplexy have occurred with orexin receptor antagonists [see Warnings and Precautions (5.3)].

Complex Sleep Behaviors

Instruct patients and their families that hypnotics may cause complex sleep behaviors, including sleepwalking, sleep driving, preparing and eating food, making phone calls, or having sex while not being fully awake. Tell patients to discontinue QUVIVIQ and notify their healthcare provider immediately if they develop any of these symptoms [see Warnings and Precautions (5.4)].

Concomitant Medications

Ask patients about alcohol consumption, medicines they are taking, and drugs they may be taking without a prescription. Advise patients to avoid consuming alcohol with QUVIVIQ [see Warnings and Precautions (5.1), Drug Interactions (7.1), Clinical Pharmacology (12.2)].

Pregnancy

Advise patients that there is a pregnancy exposure registry that monitors pregnancy outcomes in women exposed to QUVIVIQ during pregnancy [see Use in Specific Populations (8.1)].

Tolerance, Abuse, and Dependence

Tell patients not to increase the dose of QUVIVIQ on their own, and to inform you if they believe the drug "does not work" [see Drug Abuse and Dependence (9)].

Distributed by:

Idorsia Pharmaceuticals US Inc.
One Radnor Corporate Center, Suite 101
100 Matsonford Rd
Radnor, PA 19087

IDRSQUPI09302024

Patent: www.idorsia.com/patents

MEDICATION GUIDE
QUVIVIQ® (cue-VIH-vick)
(daridorexant)
tablets, for oral use, CIV

What is the most important information I should know about QUVIVIQ?
QUVIVIQ may cause serious side effects, including:

- Decreased awareness and alertness. The morning after you take QUVIVIQ, your ability to drive safely and think clearly may be decreased. You may also have sleepiness during the day. Sleepiness may increase your risk for falls.
  - Do not take more QUVIVIQ than prescribed.
  - Do not take QUVIVIQ unless you are able to stay in bed for a full night (at least 7 hours) before you must be active again.
  - Take QUVIVIQ in the evening within 30 minutes before going to bed.

See "What are the possible side effects of QUVIVIQ?" for more information about side effects.

What is QUVIVIQ?

- QUVIVIQ is a prescription medicine for adults who have trouble falling asleep or staying asleep (insomnia).
- It is not known if QUVIVIQ is safe and effective for use in children.

QUVIVIQ is a federally controlled substance (CIV) because it can be abused or lead to dependence. Keep QUVIVIQ in a safe place to prevent misuse and abuse. Selling or giving away QUVIVIQ may harm others and is against the law.

Who should not take QUVIVIQ?
Do not take QUVIVIQ:

- If you fall asleep often at unexpected times (narcolepsy).
- If you are allergic to daridorexant, or any ingredients in QUVIVIQ. See the end of this Medication Guide for a complete list of ingredients in QUVIVIQ.

Before taking QUVIVIQ, tell your healthcare provider about all of your medical conditions, including if you:

- have a history of depression, mental illness, or suicidal thoughts or actions
- have a history of drug or alcohol abuse or addiction
- have a history of a sudden onset of muscle weakness (cataplexy)
- have a history of daytime sleepiness
- have lung or breathing problems, including sleep apnea
- have liver problems
- are pregnant or plan to become pregnant. It is not known if QUVIVIQ can harm your unborn baby.
  - Pregnancy Registry: There is a pregnancy registry for women who are exposed to QUVIVIQ during pregnancy. The purpose of this registry is to collect information about the health of you and your baby. For more information or to participate in the registry, call 1-833-400-9611. Talk with your healthcare provider about the risk to your unborn baby if you take QUVIVIQ during pregnancy.
- are breastfeeding or plan to breastfeed. QUVIVIQ passes into your breast milk. Talk to your healthcare provider about the best way to feed your baby during treatment with QUVIVIQ.

Tell your healthcare provider about all of the medicines you take, including prescription and over-the-counter medicines, vitamins, and herbal supplements.
Taking QUVIVIQ with certain medicines can cause serious side effects. QUVIVIQ may affect the way other medicines work and other medicines may affect the way QUVIVIQ works.
Do not take QUVIVIQ with other medicines that can make you sleepy unless your healthcare provider tells you to.
Know the medicines you take. Keep a list of them to show your healthcare provider and pharmacist when you get a new medicine.

How should I take QUVIVIQ?

- Take QUVIVIQ exactly as your healthcare provider tells you to take it.
- Do not change your dose of QUVIVIQ without first talking to your healthcare provider.
- Take QUVIVIQ one time each night, within 30 minutes before going to bed.
- Only take QUVIVIQ when you can stay in bed for a full night (at least 7 hours).
- QUVIVIQ may take longer to work if you take it with or right after a meal.
- Call your healthcare provider if your insomnia (sleep problem) worsens or is not improved within 7 to 10 days. This may mean that there is another condition causing your sleep problem.
- If you take too much QUVIVIQ, call your healthcare provider, or contact your Poison Help Line at 1-800-222-1222, or go to the nearest hospital emergency room right away.

What should I avoid while taking QUVIVIQ?

- Do not drink alcohol while taking QUVIVIQ. It can increase the effects of alcohol, which can be dangerous.
- You may still feel drowsy the next day after taking QUVIVIQ.
  - Do not drive, operate heavy machinery, do anything dangerous, or do other activities that require clear thinking if you have taken QUVIVIQ as prescribed but do not feel fully awake, you have taken QUVIVIQ and have had less than a full night of sleep (at least 7 hours), or if you have taken more QUVIVIQ than prescribed by your healthcare provider.

What are the possible side effects of QUVIVIQ?
QUVIVIQ may cause serious side effects, including:

- See "What is the most important information I should know about QUVIVIQ?"
- Worsening depression and suicidal thoughts. Call your healthcare provider right away if you have any worsening depression or thoughts of suicide or dying.
- Temporary inability to move or talk (sleep paralysis) for up to several minutes, or hallucinations while you are going to sleep or waking up.
- Temporary weakness in your legs that can happen during the day or at night.
- Complex sleep behaviors such as sleepwalking, sleep driving, preparing and eating food, making phone calls, having sex, or doing other activities while not fully awake that you may not remember the next morning. Stop taking QUVIVIQ and call your healthcare provider right away if you experience a complex sleep behavior.

The most common side effects of QUVIVIQ include headache and sleepiness or tiredness.
These are not all of the possible side effects of QUVIVIQ.
Call your doctor for medical advice about side effects. You may report side effects to FDA at 1-800-FDA-1088.

How should I store QUVIVIQ?

- Store QUVIVIQ at room temperature between 68°F to 77°F (20°C to 25°C).
- Keep QUVIVIQ and all medicines out of the reach of children.

General information about the safe and effective use of QUVIVIQ.
Medicines are sometimes prescribed for purposes other than those listed in a Medication Guide. Do not use QUVIVIQ for a condition for which it was not prescribed. Do not give QUVIVIQ to other people, even if they have the same symptoms that you have. It may harm them. You can ask your pharmacist or healthcare provider for information about QUVIVIQ that is written for health professionals.

What are the ingredients in QUVIVIQ?
Active ingredient: daridorexant hydrochloride
Inactive ingredients: croscarmellose sodium, magnesium stearate, mannitol, microcrystalline cellulose, povidone, and silicon dioxide. The tablet film coating contains: glycerin, hypromellose, iron oxide black, iron oxide red, microcrystalline cellulose, talc, titanium dioxide, and, in the 50 mg tablet only, iron oxide yellow.

Distributed by:
Idorsia Pharmaceuticals US Inc.
One Radnor Corporate Center, Suite 101
100 Matsonford Rd
Radnor, PA 19087
For more information go to QUVIVIQ.com or call 1-833-400-9611.

This Medication Guide has been approved by the U.S. Food and Drug Administration.
IDRSQUMG09302024

Revised: 9/2024

PRINCIPAL DISPLAY PANEL - 25 mg Tablet Bottle Carton

NDC 80491-7825-3

QUVIVIQ®
(daridorexant) tablets

25 mg
CIV

Rx only

For oral use

30 tablets

Dispense the accompanying
Medication Guide to each patient.

idorsia

PRINCIPAL DISPLAY PANEL - 50 mg Tablet Bottle Carton

NDC 80491-7850-3

QUVIVIQ®
(daridorexant) tablets

50 mg
CIV

Rx only

For oral use

30 tablets

Dispense the accompanying
Medication Guide to each patient.

idorsia